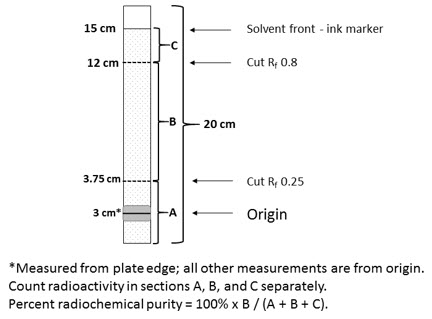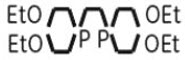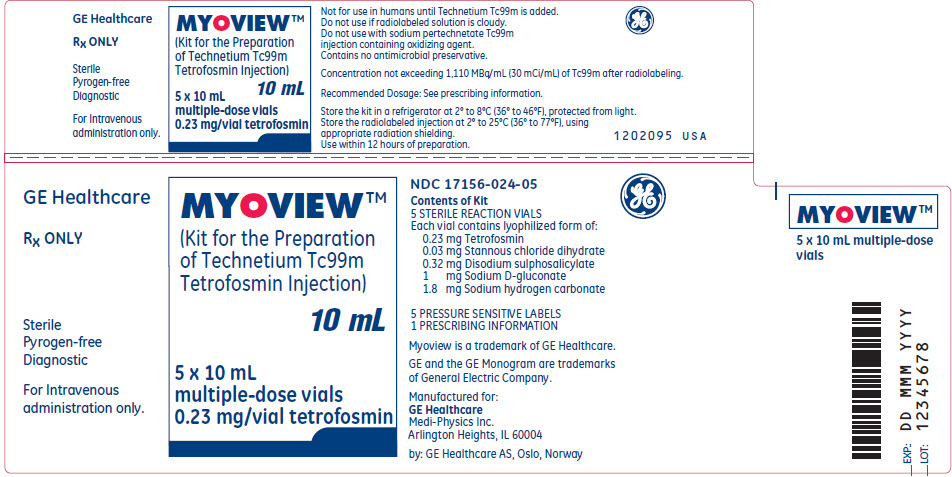 DRUG LABEL: Myoview
NDC: 17156-024 | Form: INJECTION, POWDER, LYOPHILIZED, FOR SOLUTION
Manufacturer: Medi-Physics Inc. dba GE Healthcare
Category: prescription | Type: HUMAN PRESCRIPTION DRUG LABEL
Date: 20240110

ACTIVE INGREDIENTS: Tetrofosmin 0.23 mg/1 1
INACTIVE INGREDIENTS: Stannous Chloride 0.03 mg/1 1; Disodium Sulfosalicylate 0.32 mg/1 1; Sodium Bicarbonate 1.8 mg/1 1

HIGHLIGHTS OF PRESCRIBING INFORMATION

These highlights do not include all the information needed to use MYOVIEW safely and effectively. See full prescribing information for MYOVIEW.
MYOVIEW (Kit for the preparation of technetium Tc99m tetrofosmin injection) for intravenous use
Initial U.S. Approval: 1996

1 INDICATIONS AND USAGE

MYOVIEW is a kit for the preparation of technetium Tc99m tetrofosmin for injection. Technetium Tc99m tetrofosmin injection is a radioactive diagnostic agent indicated for the following:

- Myocardial perfusion imaging under rest and/or exercise or pharmacologic stress conditions to delineate regions of reversible myocardial ischemia or infarcted myocardium in patients with known or suspected coronary artery disease (1.1)
- Assessment of left ventricular function (left ventricular ejection fraction and wall motion) in patients with known or suspected heart disease (1.2)

2 DOSAGE AND ADMINISTRATION

- Use appropriate radiation safety measures and aseptic technique during preparation and handling (2.1, 2.3)
- The recommended dose range for MYOVIEW for rest or stress imaging is 185 to 1,221 megabecquerels (MBq) [5 to 33 millicuries (mCi)] by intravenous administration (2.2)
- When rest and stress injections are administered on the same day, the first dose should be 185 to 444 MBq (5 to 12 mCi) followed by the second dose of 555 to 1,221 MBq (15 to 33 mCi) given approximately 1 to 4 hours later (2.2)
- The recommended dose range for MYOVIEW for ventricular function assessment is 185 to 1,221 MBq (5 to 33 mCi) as an intravenous injection (2.2)
- See Full Prescribing Information for instructions for preparation and determination of radiochemical purity (2.4, 2.5)
- Imaging may begin 15 minutes following administration of the agent (2.6)

3 DOSAGE FORMS AND STRENGTHS

Kit for preparation injection: lyophilized powder containing 0.23 mg tetrofosmin in a multiple-dose vial after radiolabeling with Tc99m eluate, clear solution not exceeding 1,110 MBq/mL (30 mCi/mL). (3)

4 CONTRAINDICATIONS

- None (4)

5 WARNINGS AND PRECAUTIONS

- Risk with exercise or pharmacologic stress:
  - Continuous cardiac monitoring should be performed in studying patients with known or suspected coronary artery disease (5.1)
  - When pharmacologic stress is selected as an alternative to exercise, perform the procedure in accordance with the pharmacologic stress agent's prescribing information (5.1)
- Appropriate safety measures should be used to minimize radiation exposure to clinical personnel and to the patient consistent with proper patient management (2.1, 5.2)

6 ADVERSE REACTIONS

Most common adverse reactions (incidence < 1%) after MYOVIEW injection: Cardiovascular: angina, hypertension, torsades de pointes. Gastrointestinal: vomiting, abdominal discomfort. Hypersensitivity: cutaneous allergy, hypotension, dyspnea. Special Senses: metallic taste, burning of the mouth, smell alteration. (6.1)

To report SUSPECTED ADVERSE REACTIONS, contact GE Healthcare at 1-800-654-0118 or FDA at 1-800-FDA-1088 or www.fda.gov/medwatch.

8 USE IN SPECIFIC POPULATIONS

- Advise the pregnant woman of the potential risk to the fetus based on the radiation dose from technetium Tc99m and the gestational timing of exposure (8.1)
- Lactation - A lactating woman should pump and discard breastmilk for 60 hours after technetium Tc99m tetrofosmin administration (8.2)

FULL PRESCRIBING INFORMATION

1 INDICATIONS AND USAGE

1.1 Myocardial Perfusion Imaging

Myocardial perfusion imaging under rest and/or exercise or pharmacologic stress conditions to delineate regions of reversible myocardial ischemia or infarcted myocardium in patients with known or suspected coronary artery disease.

1.2 Ventricular Function Imaging

MYOVIEW is indicated for assessment of left ventricular function (left ventricular ejection fraction and wall motion) in patients with known or suspected heart disease.

2 DOSAGE AND ADMINISTRATION

2.1 Radiation Safety – Drug Handling

Technetium Tc99m tetrofosmin is a radioactive drug and should be handled with appropriate safety measures to minimize radiation exposure during administration [see Warnings and Precautions (5.2)]. Use waterproof gloves and effective shielding, including syringe shields, when preparing and administering technetium Tc99m tetrofosmin injection.

2.2 Recommended Dosage

- The recommended dose range for MYOVIEW is 185 to 1,221 megabecquerels (MBq) (5 to 33 millicuries (mCi) by intravenous administration for rest and stress imaging.
- When rest and stress intravenous injections are administered on the same day, the first dose should be 185 to 444 MBq (5 to 12 mCi) and followed by the second dose of 555 to 1,221 MBq (15 to 33 mCi) given approximately 1 to 4 hours later.
- The recommended dose range for MYOVIEW is 185 to 1,221 MBq (5 to 33 millicuries (mCi) by intravenous administration as an intravenous injection for ventricular function assessment.

2.3 Administration Instructions

- Use aseptic technique for all drug preparation and handling.
- Measure the dose in a suitable radioactivity calibration system immediately prior to intravenous administration.
- Visually inspect the drug for particulate matter and discoloration prior to administration. Do not use or administer the drug if there is evidence of particulate matter or discoloration.
- Instruct patients to remain hydrated and void frequently following administration to decrease radiation exposure [see Warnings and Precautions (5.2)].

2.4 Instructions for Preparation

The following steps as detailed are critical and should be followed to ensure adequate preparation of the product.

1. The technetium Tc99m labeling reaction involved in the preparation of MYOVIEW Injection depends on maintaining tin in the divalent (reduced) state. Any oxidant present in the sodium pertechnetate Tc99m used may adversely affect the quality of the preparation. Sodium pertechnetate Tc99m containing oxidants should not be used for the preparation of the labeled product.
2. Elute the technetium generator with sodium chloride injection, USP.
3. Insert a venting needle (standard 18 to 26 gauge needle, not provided) through the rubber septum of the shielded vial containing the lyophilized powder.
4. Inject no more than 8.8 GBq (240 mCi) of technetium Tc99m generator eluate into the shielded vial.
5. Use sodium chloride injection, USP as a diluent. Inject 4 to 8 mL to achieve a radioactive concentration no greater than 1.1 GBq/mL (30 mCi/mL) in the vial.
6. Before removing the syringe from the vial, withdraw 2 mL of gas from above the solution.
7. Remove the venting needle.
8. Mix gently for 10 seconds to ensure complete dissolution of the powder.
9. Incubate at room temperature for 15 minutes.
10. Assay the total activity using a suitably calibrated instrument; complete the user radiation label and attach it to the vial.
11. Measure the pH of the prepared injection and verify it is between 7.5 to 9.0.
12. Store the radiolabeled MYOVIEW vial at 2° to 25°C (36° to 77°F) and use radiolabeled injection within 12 hours of preparation.

2.5 Determination of Radiochemical Purity

Obtain the following materials:

1. SA TLC strip (2 cm × 20 cm), do not heat activate
2. Ascending chromatography tank and cover
3. Mixture of acetone and dichloromethane (65:35% v/v), prepare freshly
4. Syringe (1 mL) with needle (22 to 25 gauge)
5. Suitable counting equipment

Perform the following:

1. Pour the 65:35% v/v acetone:dichloromethane mixture into the chromatography tank to a depth of 1 cm and cover the tank to allow the solvent vapor to equilibrate.
2. Mark SA TLC strip with a pencil line at 3 cm from the bottom and, using an ink marker pen, at 15 cm from the pencil line. The pencil line indicates the origin where the sample is to be applied and movement of color from the ink line will indicate the position of the solvent front when upward elution should be stopped.
3. Mark cutting positions at 3.75 cm and 12 cm above the origin [retention value (Rf) 0.25 and 0.8 respectively] in pencil.
4. Using a 1 mL syringe and needle, apply a 10 microliter sample of the prepared injection at the origin of the strip. Do not allow the spot to dry. Place the strip in the chromatography tank immediately and replace the cover. Ensure that the strip is not adhering to the walls of the tank.
  Note: A 10 microliter sample will produce a spot with a diameter of approximately 10 mm. Different sample volumes have been shown to give unreliable radiochemical purity values.
5. When the solvent reaches the ink line, remove the strip from the tank and allow it to dry.
6. Cut the strip into 3 pieces at the marked cutting positions and measure the activity on each using suitable counting equipment. Ensure similar counting geometry for each piece and minimize equipment dead time losses. Note: Free Tc99m pertechnetate runs to the top piece of the strip. MYOVIEW runs to the center piece of the strip. Reduced hydrolyzed Tc99m and any hydrophilic complex impurities remain at the origin in the bottom piece of the strip.
  TLC strip diagram
7. Calculate the radiochemical purity from:
  % Tc99m tetrofosmin = | Activity of Center Piece (B) | × 100
   | Total Activity of Three Pieces (A+B+C) | × 100
8. Do not use material if the radiochemical purity is less than 90%.

2.6 Imaging Instructions

- Imaging may begin 15 minutes after injection.
- The recommended imaging duration of the scan may vary depending on dose, imaging acquisition, and reconstruction parameters.

2.7 Radiation Dosimetry

Radiation absorbed dose per unit activity of the agent injected intravenously in an adult of average weight (74 kg) is estimated in Table 1 for exercise and resting conditions. The values listed correspond to a 3.5-hour voiding period for excretion from the urinary bladder.

Table 1 Estimated Radiation Absorbed Dose (Technetium Tc99m Tetrofosmin Injection)
 | Radiation absorbed dose per unit activity injected intravenously
 | Exercise |  | Rest
Target organ | rad/mCi | microGy/MBq | rad/mCi | microGy/MBq
Gall bladder wall | 0.10 | 27 | 0.13 | 36
Upper large intestine | 0.074 | 20 | 0.10 | 27
Lower large intestine | 0.055 | 15 | 0.074 | 20
Bladder wall | 0.052 | 14 | 0.063 | 17
Small intestine | 0.041 | 11 | 0.056 | 15
Kidney | 0.037 | 10 | 0.048 | 13
Salivary glands | 0.030 | 8.0 | 0.043 | 12
Ovaries | 0.029 | 7.7 | 0.033 | 8.8
Uterus | 0.026 | 7.0 | 0.029 | 7.8
Bone surface | 0.023 | 6.3 | 0.021 | 5.8
Thyroid | 0.017 | 4.7 | 0.020 | 5.5
Pancreas | 0.019 | 5.0 | 0.018 | 4.9
Heart wall | 0.019 | 5.2 | 0.017 | 4.7
Stomach | 0.017 | 4.6 | 0.017 | 4.5
Adrenals | 0.016 | 4.4 | 0.016 | 4.2
Liver | 0.012 | 3.3 | 0.015 | 4.0
Spleen | 0.015 | 4.1 | 0.014 | 3.9
Red marrow | 0.014 | 3.9 | 0.014 | 3.8
Muscle | 0.013 | 3.5 | 0.012 | 3.3
Testes | 0.013 | 3.4 | 0.011 | 3.1
Thymus | 0.012 | 3.3 | 0.010 | 2.8
Esophagus | 0.012 | 3.3 | 0.010 | 2.8
Lungs | 0.012 | 3.2 | 0.010 | 2.8
Brain | 0.010 | 2.7 | 0.0085 | 2.3
Skin | 0.0081 | 2.2 | 0.0074 | 2.0
Breasts | 0.0085 | 2.3 | 0.0074 | 2.0
Remaining organs | 0.014 | 3.8 | 0.014 | 3.8
Effective dose per unit activity | 0.026 rem/mCi | 6.9 microSv/MBq | 0.030 rem/mCi | 8.0 microSv/MBq

3 DOSAGE FORMS AND STRENGTHS

Kit for the preparation of technetium Tc99m tetrofosmin injection: 10 mL multiple-dose, clear, glass vial with a white sterile, non-pyrogenic, lyophilized powder of 0.23 mg tetrofosmin, 0.03 mg stannous chloride dihydrate, 0.32 disodium sulphosalicylate, 1 mg sodium D-gluconate and 1.8 mg sodium hydrogen carbonate.

Following radiolabeling with the Tc99m eluate, MYOVIEW is a clear solution not exceeding 1,110 MBq/mL (30 mCi/mL) of Tc99m.

4 CONTRAINDICATIONS

None.

5 WARNINGS AND PRECAUTIONS

5.1 Risks Associated with Exercise or Pharmacologic Stress

Patients evaluated with exercise or pharmacologic stress may experience serious adverse reactions such as myocardial infarction, arrhythmia, hypotension, bronchoconstriction, and cerebrovascular reactions such as headache, paraesthesias, convulsions, somnolence and cerebrovascular accident, including hemorrhage. Perform stress testing in the setting where cardiac resuscitation equipment and trained staff are readily available. When pharmacologic stress is selected as an alternative to exercise, perform the procedure in accordance with the pharmacologic stress agent's prescribing information.

5.2 Radiation Risks

Technetium Tc99m contributes to a patient's overall long-term cumulative radiation exposure. Long-term cumulative radiation exposure is associated with an increased risk of cancer. Ensure safe handling and preparation radiolabeling procedures to protect patients and health care workers from unintentional radiation exposure. Encourage adequate hydration; instruct patients to void when the examination is completed and as often thereafter as possible [see Dosage and Administration (2.1) and (2.3)].

5.3 Hypersensitivity Reactions

Hypersensitivity reactions including anaphylaxis, dyspnea, bronchospasm, throat tightness, coughing, tachycardia, chest pain, hypotension, abdominal pain, and cutaneous reactions (rash, urticaria, pruritus, erythema, and swelling or angioedema) have been observed after the administration of MYOVIEW. Always have cardiopulmonary resuscitation equipment and personnel available and monitor all patients for hypersensitivity reactions.

6 ADVERSE REACTIONS

The following clinically significant adverse reactions are described elsewhere in the labeling:

- Hypersensitivity Reactions [see Warnings and Precautions (5.3)]

6.1 Clinical Trials Experience

Because clinical trials are conducted under widely varying conditions, adverse reaction rates observed in the clinical trials of MYOVIEW cannot be directly compared to rates in the clinical trials of another drug and may not reflect the rates observed in practice.

Adverse reactions were evaluated in clinical studies (using an exercise/rest protocol) of 764 adults (511 men and 253 women) with a mean age of 58.7 years (range 29 to 94 years). The subjects received a mean dose of 285 MBq (7.7 mCi) on the first injection and 829 MBq (22.4 mCi) on the second injection of MYOVIEW.

After MYOVIEW injection, angina occurred in 4 subjects, ventricular tachycardia in 1 subject, and respiratory arrest in 1 subject.

The following reactions were noted in less than 1% of subjects:

Cardiovascular: angina, hypertension, torsades de pointes.

Gastrointestinal: vomiting, abdominal discomfort.

Hypersensitivity: cutaneous allergy, hypotension, dyspnea.

Special Senses: metallic taste, burning of the mouth, smell alteration.

In four studies, 438 adults (232 men and 205 women: gender was not recorded for one subject) with a mean age of 65 years (range 27 to 97 years) received a single pharmacologic stress agent. The subjects received a mean dose of 7 to 8 mCi on the rest/first injection and 22 to 34 mCi on the stress/second injection. Among the 438 subjects, 319 subjects (73%) experienced an adverse reaction. Reactions occurring in ≥1% of the subjects included angina (39%), flushing (36%), dyspnea (28%), headache (14%), abdominal pain (11%), dizziness (7%), palpitations (2%), nausea (2%), hypotension (1%) and pain (1%). Events occurring in <1% include cough, arrhythmia, bronchospasm, ECG abnormalities, hypertension, vomiting and asthenia.

6.2 Postmarketing Experience

The following adverse reactions have been identified during post approval use of MYOVIEW. Because these reactions are reported voluntarily from a population of uncertain size, it is not always possible to reliably estimate their frequency or establish a causal relationship to drug exposure.

The most common adverse reactions reported included: rash, urticaria, abnormal vision, hypersensitivity reactions, and fever.

8 USE IN SPECIFIC POPULATIONS

8.1 Pregnancy

Risk Summary

There are no data with technetium Tc99m tetrofosmin use in pregnant women to inform any drug associated risks. Animal reproduction studies with technetium Tc99m tetrofosmin have not been conducted. However, all radiopharmaceuticals have the potential to cause fetal harm depending on the fetal stage of development and the magnitude of the radiation dose. If considering technetium Tc99m tetrofosmin administration to a pregnant woman advise the pregnant woman of risk to the fetus.

The estimated background risk of major birth defects and miscarriage for the indicated population is unknown. All pregnancies have a background risk of birth defect, loss, or other adverse outcomes. In the U.S. general population, the estimated background risk of major birth defects and miscarriage in clinically recognized pregnancies is 2 to 4% and 15 to 20%, respectively.

8.2 Lactation

Risk Summary

Technetium Tc99m tetrofosmin is present in human milk in small amounts (<1% of maternal dose). There are no data available regarding the effects of technetium Tc99m tetrofosmin on the breastfed infant or on milk production. The developmental and health benefits of breastfeeding should be considered along with the mother's clinical need for MYOVIEW and any potential adverse effects on the breastfed child from MYOVIEW or from the underlying maternal condition.

Clinical Considerations

To decrease radiation exposure to the breastfed infant, advise a lactating woman to pump and discard breast milk for 60 hours (10 half-lives) after technetium Tc99m tetrofosmin administration.

8.4 Pediatric Use

Safety and effectiveness in pediatric patients have not been established.

8.5 Geriatric Use

Of 2,300 subjects in clinical studies of MYOVIEW, 1,053 (46%) were 65 or older and 270 (12%) were 75 or older. No overall differences in safety were observed between these subjects and younger subjects, and other reported clinical experience has not identified differences in responses between elderly and younger patients, but greater sensitivity of some older individuals cannot be ruled out.

11 DESCRIPTION

11.1 Chemical Characteristics

MYOVIEW is a kit for the preparation of technetium Tc99m tetrofosmin injection for intravenous use. Technetium Tc99m tetrofosmin is a radioactive diagnostic agent. Each multiple-dose 10 mL glass vial contains a sterile, non-pyrogenic, lyophilized powder of 0.23 mg tetrofosmin [6,9-bis(2-ethoxyethyl)-3,12-dioxa-6,9-diphosphatetradecane], 0.03 mg stannous chloride dihydrate, (minimum stannous tin 0.015 mg; total stannous and stannic tin 0.0522 mg) 0.32 mg disodium sulphosalicylate, 1 mg sodium D-gluconate, and 1.8 mg sodium hydrogen carbonate. The lyophilized powder is sealed under a nitrogen atmosphere with a rubber closure. The product contains no antimicrobial preservative. The chemical formula of tetrofosmin is C18H40O4P2 with the following structural formula:

C18H40O4P2

When sterile, pyrogen-free sodium pertechnetate Tc99m in isotonic saline is added to the vial, a Tc99m complex of tetrofosmin is formed. The radiolabeled product is a clear solution and the pH is in the range of 7.5 to 9.0.

11.2 Physical Characteristics

Technetium Tc99m decays by isomeric transition with a physical half-life of 6 hours. Photons that are useful for imaging studies are listed in Table 2.

Table 2 Principal radiation emission data - technetium Tc99m
Radiation | Mean % disintegration | Mean energy (keV)
Gamma 2 | 88.5 | 140.5

11.3 External Radiation

The air-kerma-rate (exposure-rate) constant for technetium Tc99m is 5.23 m^2∙pGy∙(MBq)^−1∙s^−1 [0.795 cm^2∙R∙(mCi)^−1∙h^−1].

A range of values for the relative radiation attenuation by various thicknesses of Pb shielding is shown in Table 3. For example, the use of 3 mm thick Pb will decrease the external radiation exposure by a factor of approximately 1,000.

Table 3 Radiation attenuation by lead shielding
Shield thickness (Pb) mm | Factor of attenuation
0.25 | 0.5
1 | 10^-1
2 | 10^-2
3 | 10^-3
4 | 10^-4
5 | 10^-5

To correct for physical decay of this radionuclide, the fractions that remain at selected intervals relative to the time of calibration are shown in Table 4.

Table 4 Physical decay chart - Tc99m half-life 6 hours
Hours | Fraction Remaining | Hours | Fraction Remaining
0 [Calibration time (time of preparation)] | 1.000 | 7 | 0.446
1 | 0.891 | 8 | 0.397
2 | 0.794 | 9 | 0.354
3 | 0.707 | 10 | 0.315
4 | 0.630 | 11 | 0.281
5 | 0.562 | 12 | 0.250
6 | 0.500 | 24 | 0.063

12 CLINICAL PHARMACOLOGY

12.1 Mechanism of Action

Technetium (99mTc) tetrofosmin is a lipophilic, cationic complex which diffuses passively through the cell membrane and is locally retained actively due to the presence of intact mitochondria reflecting the presence of viable cells. After intravenous injection, it is distributed within the myocardium according to myocardial perfusion and viability.

12.2 Pharmacodynamics

The relationship between Tc99m tetrofosmin plasma concentrations and successful imaging has not been explored in clinical trials.

12.3 Pharmacokinetics

Uptake in the myocardium is dependent on coronary flow and reaches a maximum of 1.2% of the injected dose (i.d.) at 5 minutes and 1% of the i.d. at 2 hours, respectively. Background activities in the blood, liver and lung were less than 5% of the administered activity in whole blood at 10 minutes post-injection, less than 4.5% i.d., after 60 minutes, and less than 2% i.d. after 30 minutes.

Elimination

Approximately 66% of the injected activity is excreted within 48 hours post-injection, with approximately 40% excreted in the urine and 26% in the feces.

13 NONCLINICAL TOXICOLOGY

13.1 Carcinogenesis, Mutagenesis, Impairment of Fertility

Studies have not been conducted to evaluate carcinogenic potential or effects on fertility. Tetrofosmin sulphosalicylate was not mutagenic in vitro in the Ames test, mouse lymphoma, or human lymphocyte tests, nor was it clastogenic in vivo in the mouse micronucleus test.

14 CLINICAL STUDIES

14.1 Exercise/Resting Myocardial Perfusion Imaging Studies

A total of 252 subjects with ischemic heart disease or atypical chest pain were studied in two open-label, multi-center, clinical studies (study a and study b). Of these 252 subjects there were 212 (84%) males and 40 (16%) females with a mean age of 60.5 years (range 33.7 to 82.4 years).

All subjects had exercise and rest planar imaging with MYOVIEW and thallium-201; 191 (76%) subjects also had single photon emission computed tomography (SPECT) imaging. At peak exercise, maximum heart rate achieved and peak systolic blood pressure were comparable after MYOVIEW and thallium-201 exercise studies. The MYOVIEW and thallium-201 images were separated by a mean of 5.1 days (1 to 14 days before or 2 to 14 days after MYOVIEW). For MYOVIEW imaging, each subject received 185 to 296 MBq (5 to 8 mCi) Tc99m tetrofosmin at peak exercise and 555 to 888 MBq (15 to 24 mCi) Tc99m tetrofosmin at rest approximately 4 hours later. For thallium-201 imaging, subjects received thallium-201 55.5 to 74 MBq (1.5 to 2 mCi) at peak exercise.

The images were evaluated for the quality of the image (excellent, good or poor) and the diagnosis (with scores of 0 = normal, 1 = ischemia, 2 = infarct, 3 = mixed infarct and ischemia). The primary outcome variable was the percentage of correct diagnoses in comparison to the final clinical diagnosis. All planar images were blindly read; SPECT images were evaluated by the unblinded investigator. The results for each blinded reader are noted in Table 5.

Table 5 Overall Diagnostic Outcome
 |  | Thallium 201 |  | MYOVIEW
 |  | Reader 1 | Reader 2 | Reader 1 | Reader 2
Diagnosis | Study | % (95% CI) | % (95% CI) | % (95% CI) | % (95% CI)
Ischemia | a | 77.7 (68.8, 85.0) | 75.0 (65.9, 82.7) | 66.3 (56.7, 75.1) | 63.6 (53.9, 72.6)
 | b | 75.6 (66.9, 83.0) | 68.9 (59.8, 77.1) | 66.4 (57.2, 74.8) | 66.4 (57.2, 74.8)
Infarct | a | 75.9 (66.9, 83.5) | 75.0 (65.9, 82.7) | 74.5 (65.4, 82.4) | 75.5 (66.3, 83.2)
 | b | 70.6 (61.5, 78.6) | 69.7 (60.7, 77.8) | 73.1 (64.2, 80.8) | 68.1 (58.9, 76.3)

14.2 Pharmacological Stress Myocardial Perfusion Imaging Studies

MYOVIEW imaging after pharmacologic stress was evaluated in two studies in subjects with known or suspected coronary artery disease (CAD). Three blinded reads were obtained for 57 subjects (45 male [79%], 12 female [21%]; mean age 60.1 years) all of whom had angiography. Subject level analyses were based on the finding of SPECT myocardial perfusion abnormalities in patients with angiographically confirmed disease. Subject level sensitivities for MYOVIEW ranged from 68 to 83% and subject level specificities ranged from 45 to 82% across readers and studies.

14.3 Ventricular Function Stress Myocardial Perfusion Imaging Studies

Two open-label, multicenter, identically designed, blinded image read studies were conducted to assess left ventricular function using MYOVIEW ECG gated SPECT (GSPECT) myocardial perfusion imaging. A total of 329 subjects (216 male [65.7%], 113 female [34.3%]); mean age of 60.4 years) with known or suspected heart disease or requiring ventricular function assessments were dosed with MYOVIEW. Of these, 297 were considered evaluable. MYOVIEW was administered at rest and at peak stress using either a one-day or a 2-day dosing protocol.

For both studies, all subjects' stress GSPECT exams were compared to the reference exam of radionuclide ventriculography with Tc99m labeled RBCs (multiple gated acquisition [MUGA]), performed 1 to 5 days after the second MYOVIEW injection. All subjects' GSPECT exams were assessed by 3 independent blinded readers per study. The MUGA exams were evaluated by an independent consensus panel composed of 3 blinded readers. Subject level assessments were based upon discrimination between normal and abnormal values for LVEF (LVEF ≥50% was considered normal) and normal and abnormal wall motion as judged visually. Sensitivity and specificity of LVEF determinations ranged from 81% to 88% and 76% to 85% respectively across studies and readers. Sensitivity and specificity of wall motion determinations ranged from 80% to 92% and 68% to 86% respectively across studies and readers.

16 HOW SUPPLIED/STORAGE AND HANDLING

16.1 How supplied

Five (5) multiple-dose kits, each containing a 10 mL glass vial with a sterile, non-pyrogenic, lyophilized powder containing 0.23 mg tetrofosmin, 0.03 mg stannous chloride dihydrate, 0.32 mg disodium sulphosalicylate, 1 mg sodium D-gluconate, 1.8 mg sodium hydrogen carbonate.

NDC 17156-024-05

The radionuclide is not part of the kit. Before radiolabeling with Tc99m, the contents of the kit are not radioactive.

16.2 Storage and Handling

Store the kit at 2° to 8°C (36° to 46°F), protected from light.

Store the radiolabeled vial at 2° to 25°C (36° to 77°F), using appropriate radiation shielding. Use within 12 hours of preparation.

This reagent kit is approved for use by persons under license by the Nuclear Regulatory Commission or the relevant regulatory authority of an Agreement State; store and dispose of technetium Tc99m tetrofosmin in accordance with these regulations.

17 PATIENT COUNSELING INFORMATION

- Instruct patients to remain hydrated and void frequently following administration to decrease radiation exposure.
- Advise a lactating woman to pump and discard breast milk for 60 hours (10 half-lives) after technetium Tc99m tetrofosmin administration to decrease radiation exposure to the breastfed infant.

Manufactured by:
GE Healthcare AS
Oslo, Norway

Distributed by:
GE Healthcare
Medi-Physics, Inc.
Arlington Heights, IL 60004

MYOVIEW is a trademark of GE Healthcare

GE and the GE Monogram are trademarks of General Electric Company.

© 2022 General Electric Company - All rights reserved.

PRINCIPAL DISPLAY PANEL - 5 Vial Kit Label

MYOVIEW™

(Kit for the Preparation
of Technetium Tc99m
Tetrofosmin Injection)

10 mL

5 x 10 mL
multiple-dose vials
0.23 mg/vial tetrofosmin